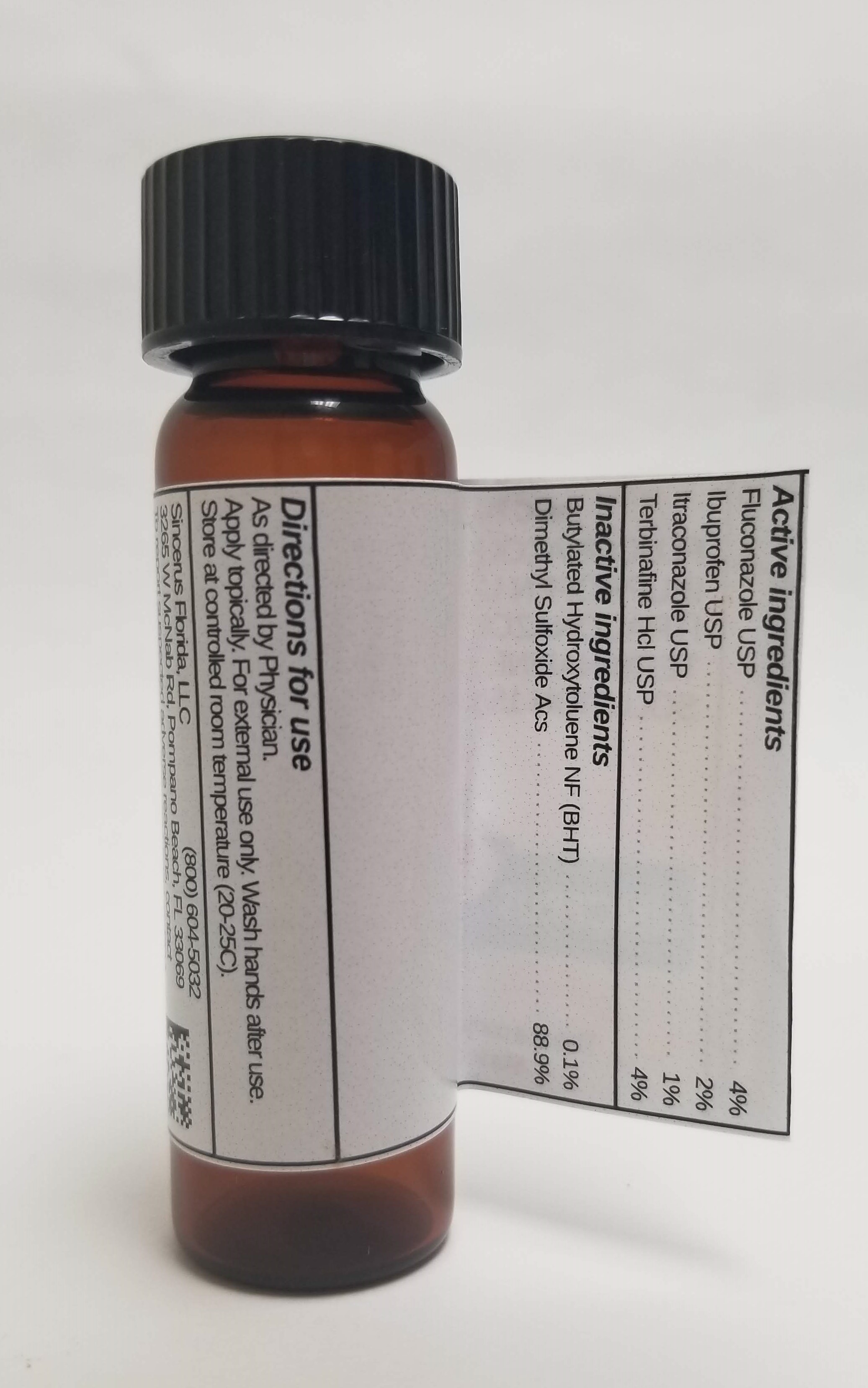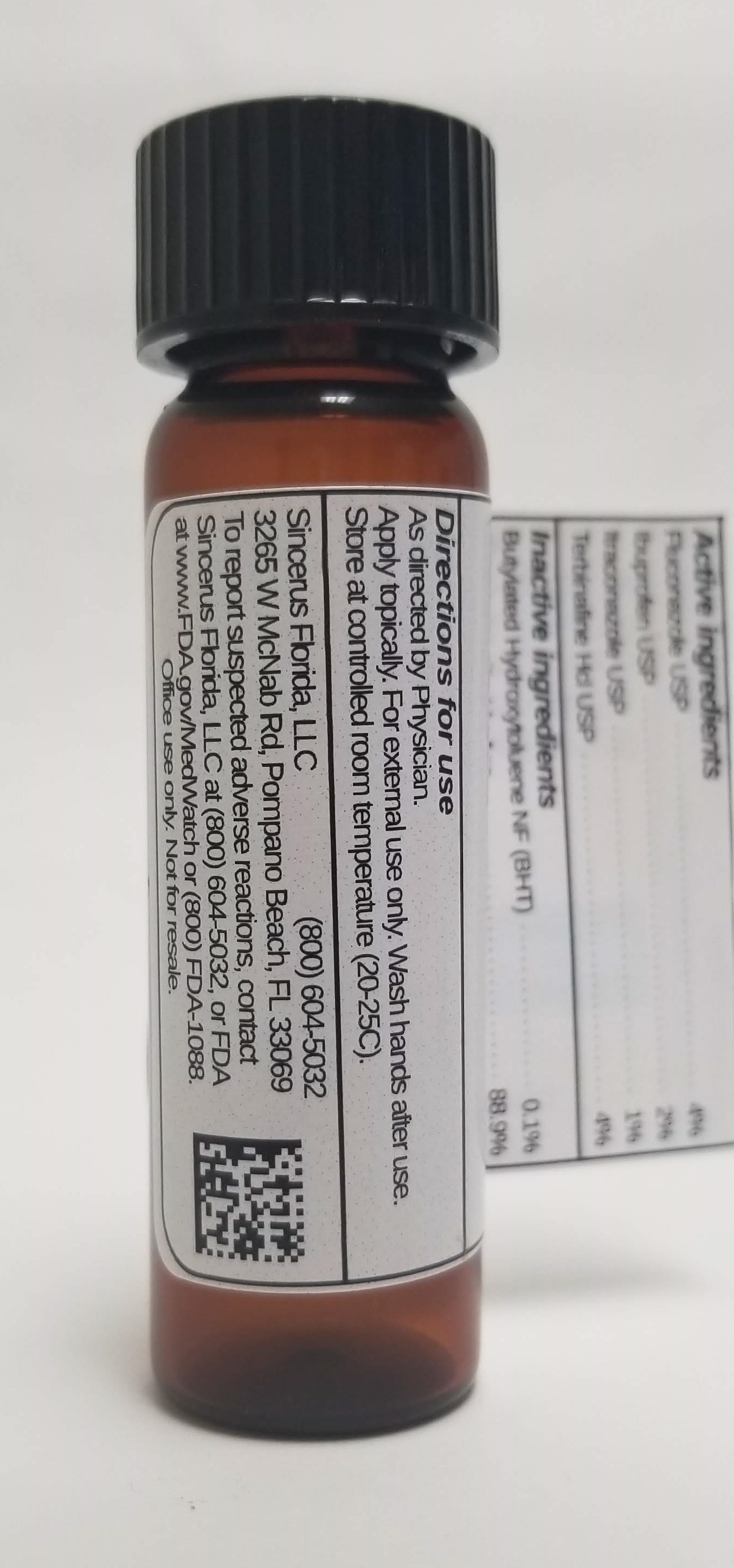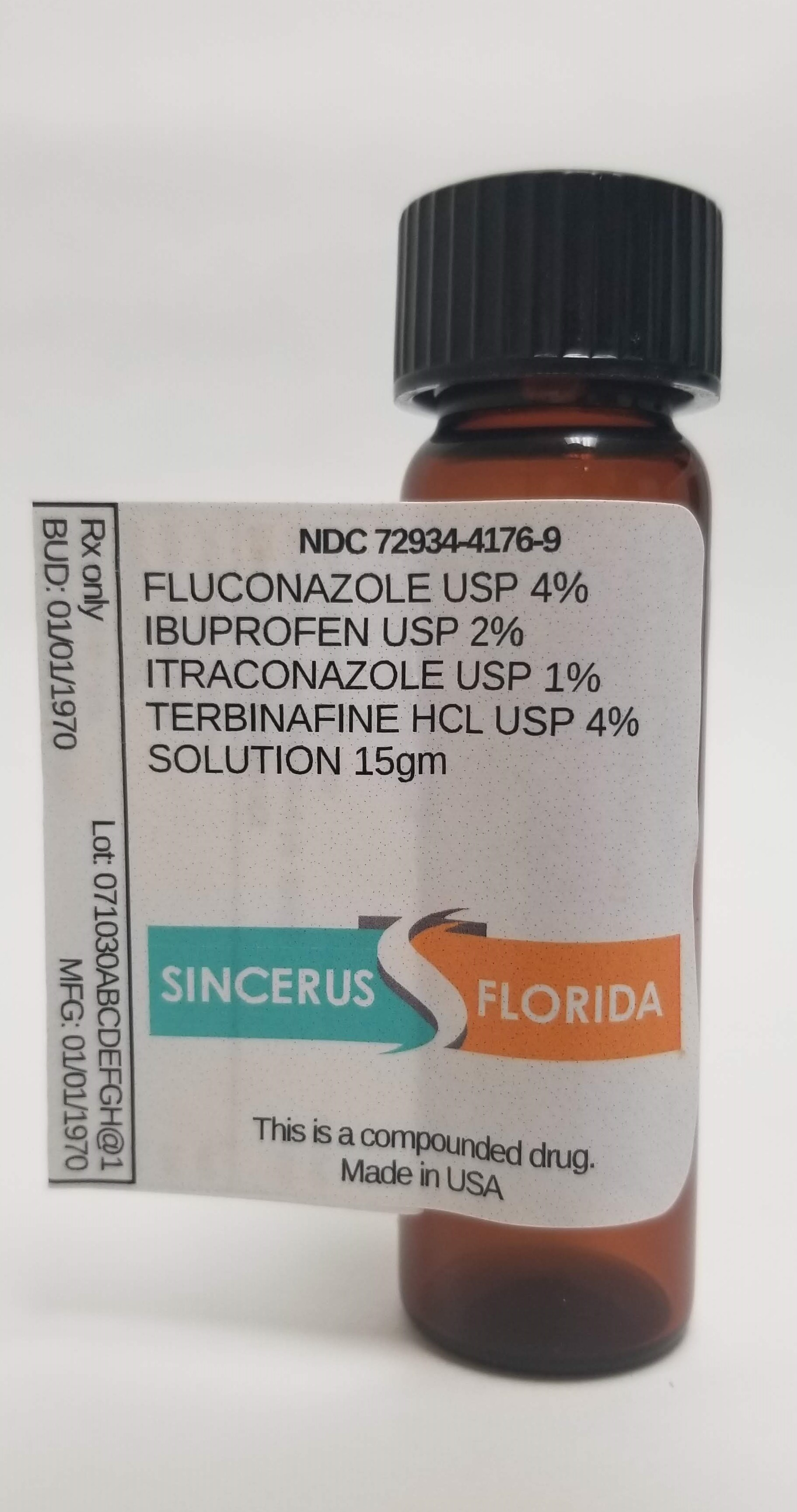 DRUG LABEL: FLUCONAZOLE 4% / IBUPROFEN 2% / ITRACONAZOLE 1% / TERBINAFINE HCL 4%
NDC: 72934-4176 | Form: SOLUTION
Manufacturer: Sincerus Florida, LLC
Category: prescription | Type: HUMAN PRESCRIPTION DRUG LABEL
Date: 20190424

ACTIVE INGREDIENTS: IBUPROFEN 2 g/100 g; ITRACONAZOLE 1 g/100 g; TERBINAFINE 4 g/100 g; FLUCONAZOLE 4 g/100 g

FLUCONAZOLE 4% / IBUPROFEN 2% / ITRACONAZOLE 1% / TERBINAFINE HCL 4%